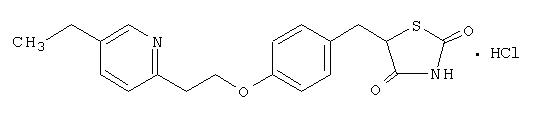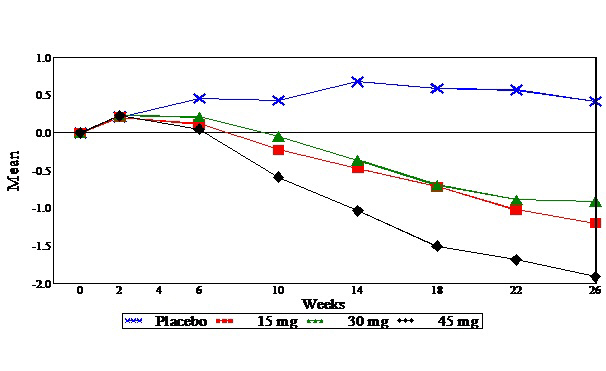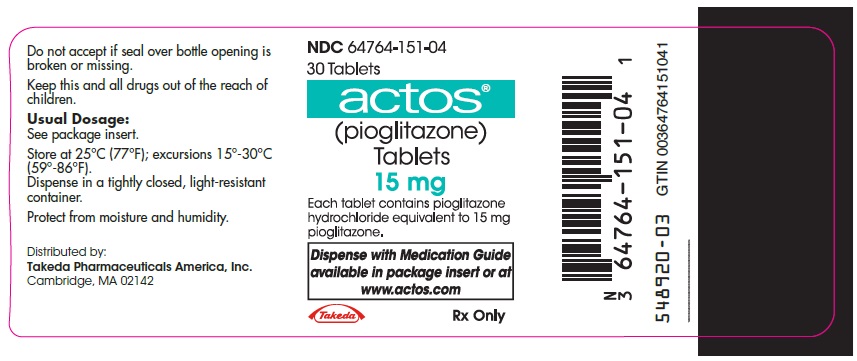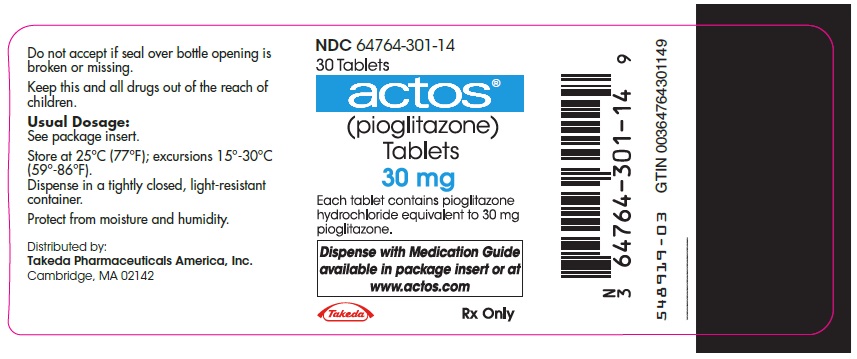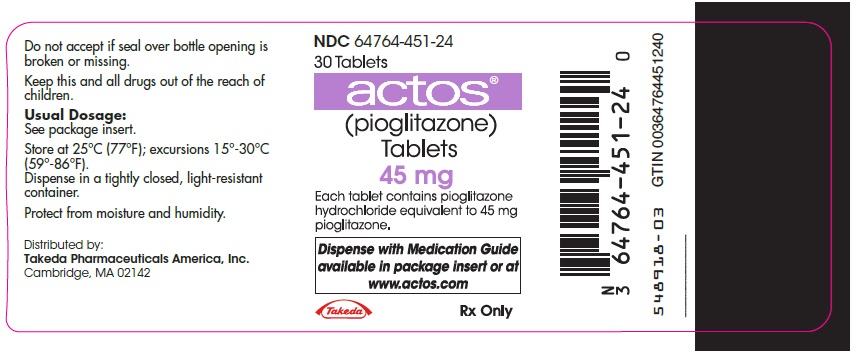 DRUG LABEL: Actos
NDC: 64764-151 | Form: TABLET
Manufacturer: Takeda Pharmaceuticals America, Inc.
Category: prescription | Type: HUMAN PRESCRIPTION DRUG LABEL
Date: 20250328

ACTIVE INGREDIENTS: PIOGLITAZONE HYDROCHLORIDE 15 mg/1 1
INACTIVE INGREDIENTS: carboxymethylcellulose calcium; HYDROXYPROPYL CELLULOSE (1600000 WAMW); lactose monohydrate; magnesium stearate

HIGHLIGHTS OF PRESCRIBING INFORMATION

These highlights do not include all the information needed to use ACTOS® safely and effectively. See full prescribing information for ACTOS.
ACTOS (pioglitazone) tablets for oral use
Initial U.S. Approval: 1999

WARNING: CONGESTIVE HEART FAILURE

See full prescribing information for complete boxed warning.

- Thiazolidinediones, including ACTOS, cause or exacerbate congestive heart failure in some patients. (5.1)
- After initiation of ACTOS, and after dose increases, monitor patients carefully for signs and symptoms of heart failure (e.g., excessive, rapid weight gain, dyspnea, and/or edema). If heart failure develops, it should be managed according to current standards of care and discontinuation or dose reduction of ACTOS must be considered. (5.1)
- ACTOS is not recommended in patients with symptomatic heart failure. (5.1)
- Initiation of ACTOS in patients with established New York Heart Association (NYHA) Class III or IV heart failure is contraindicated. (4, 5.1)

1 INDICATIONS AND USAGE

ACTOS is a thiazolidinedione and an agonist for peroxisome proliferator-activated receptor (PPAR) gamma indicated as an adjunct to diet and exercise to improve glycemic control in adults with type 2 diabetes mellitus in multiple clinical settings. (1, 14)

Important Limitations of Use:

- Not for treatment of type 1 diabetes or diabetic ketoacidosis. (1)

2 DOSAGE AND ADMINISTRATION

- Initiate ACTOS at 15 mg or 30 mg once daily. Limit initial dose to 15 mg once daily in patients with NYHA Class I or II heart failure. (2.1)
- If there is inadequate glycemic control, the dose can be increased in 15 mg increments up to a maximum of 45 mg once daily. (2.1)
- Obtain liver tests before starting ACTOS. If abnormal, use caution when treating with ACTOS, investigate the probable cause, treat (if possible) and follow appropriately. Monitoring liver tests while on ACTOS is not recommended in patients without liver disease. (5.3)

3 DOSAGE FORMS AND STRENGTHS

Tablets: 15 mg, 30 mg, and 45 mg (3)

4 CONTRAINDICATIONS

- Initiation in patients with established New York Heart Association (NYHA) Class III or IV heart failure [see Boxed Warning]. (4)
- Use in patients with known hypersensitivity to pioglitazone or any other component of ACTOS. (4)

5 WARNINGS AND PRECAUTIONS

- Congestive heart failure: Fluid retention may occur and can exacerbate or lead to congestive heart failure. Combination use with insulin and use in congestive heart failure NYHA Class I and II may increase risk. Monitor patients for signs and symptoms. (5.1)
- Hypoglycemia: When used with insulin or an insulin secretagogue, a lower dose of the insulin or insulin secretagogue may be needed to reduce the risk of hypoglycemia. (5.2)
- Hepatic effects: Postmarketing reports of hepatic failure, sometimes fatal. Causality cannot be excluded. If liver injury is detected, promptly interrupt ACTOS and assess patient for probable cause, then treat cause if possible, to resolution or stabilization. Do not restart ACTOS if liver injury is confirmed and no alternate etiology can be found. (5.3)
- Bladder cancer: May increase the risk of bladder cancer. Do not use in patients with active bladder cancer. Use caution when using in patients with a prior history of bladder cancer. (5.4)
- Edema: Dose-related edema may occur. (5.5)
- Fractures: Increased incidence in female patients. Apply current standards of care for assessing and maintaining bone health. (5.6)
- Macular edema: Postmarketing reports. Recommend regular eye exams in all patients with diabetes according to current standards of care with prompt evaluation for acute visual changes. (5.7)
- Macrovascular outcomes: There have been no clinical studies establishing conclusive evidence of macrovascular risk reduction with ACTOS. (5.8)

6 ADVERSE REACTIONS

Most common adverse reactions (≥5%) are upper respiratory tract infection, headache, sinusitis, myalgia, and pharyngitis. (6.1)

To report SUSPECTED ADVERSE REACTIONS, contact Takeda Pharmaceuticals America, Inc. at 1-877-TAKEDA-7 (1-877-825-3327) or FDA at 1-800-FDA-1088 or www.fda.gov/medwatch.

7 DRUG INTERACTIONS

- Strong CYP2C8 inhibitors (e.g., gemfibrozil) increase pioglitazone concentrations. Limit ACTOS dose to 15 mg daily. (2.3, 7.1)
- CYP2C8 inducers (e.g., rifampin) may decrease pioglitazone concentrations. (7.2)
- Topiramate may decrease pioglitazone concentrations. (7.3)

8 USE IN SPECIFIC POPULATIONS

- Females and Males of Reproductive Potential: Advise premenopausal females of the potential for an unintended pregnancy. (8.3)
- Pediatrics: Not recommended for use in pediatric patients. (8.4)

FULL PRESCRIBING INFORMATION

WARNING: CONGESTIVE HEART FAILURE

- Thiazolidinediones, including ACTOS®, cause or exacerbate congestive heart failure in some patients [see Warnings and Precautions (5.1)].
- After initiation of ACTOS, and after dose increases, monitor patients carefully for signs and symptoms of heart failure (e.g., excessive, rapid weight gain, dyspnea, and/or edema). If heart failure develops, it should be managed according to current standards of care and discontinuation or dose reduction of ACTOS must be considered.
- ACTOS is not recommended in patients with symptomatic heart failure.
- Initiation of ACTOS in patients with established New York Heart Association (NYHA) Class III or IV heart failure is contraindicated [see Contraindications (4) and Warnings and Precautions (5.1)].

1 INDICATIONS AND USAGE

Monotherapy and Combination Therapy

ACTOS is indicated as an adjunct to diet and exercise to improve glycemic control in adults with type 2 diabetes mellitus in multiple clinical settings [see Clinical Studies (14)].

Important Limitations of Use

ACTOS exerts its antihyperglycemic effect only in the presence of endogenous insulin. ACTOS should not be used to treat type 1 diabetes or diabetic ketoacidosis, as it would not be effective in these settings.

Use caution in patients with liver disease [see Warnings and Precautions (5.3)].

2 DOSAGE AND ADMINISTRATION

2.1 Recommendations for All Patients

ACTOS should be taken once daily and can be taken without regard to meals.

The recommended starting dose for patients without congestive heart failure is 15 mg or 30 mg once daily.

The recommended starting dose for patients with congestive heart failure (NYHA Class I or II) is 15 mg once daily.

The dose can be titrated in increments of 15 mg up to a maximum of 45 mg once daily based on glycemic response as determined by HbA1c.

After initiation of ACTOS or with dose increase, monitor patients carefully for adverse reactions related to fluid retention such as weight gain, edema, and signs and symptoms of congestive heart failure [see Boxed Warning and Warnings and Precautions (5.5)].

Liver tests (serum alanine and aspartate aminotransferases, alkaline phosphatase, and total bilirubin) should be obtained prior to initiating ACTOS. Routine periodic monitoring of liver tests during treatment with ACTOS is not recommended in patients without liver disease. Patients who have liver test abnormalities prior to initiation of ACTOS or who are found to have abnormal liver tests while taking ACTOS should be managed as described under Warnings and Precautions [see Warnings and Precautions (5.3) and Clinical Pharmacology (12.3)].

2.2 Concomitant Use with an Insulin Secretagogue or Insulin

If hypoglycemia occurs in a patient co-administered ACTOS and an insulin secretagogue (e.g., sulfonylurea), the dose of the insulin secretagogue should be reduced.

If hypoglycemia occurs in a patient co-administered ACTOS and insulin, the dose of insulin should be decreased by 10% to 25%. Further adjustments to the insulin dose should be individualized based on glycemic response.

2.3 Concomitant Use with Strong CYP2C8 Inhibitors

Coadministration of ACTOS and gemfibrozil, a strong CYP2C8 inhibitor, increases pioglitazone exposure approximately 3-fold. Therefore, the maximum recommended dose of ACTOS is 15 mg daily when used in combination with gemfibrozil or other strong CYP2C8 inhibitors [see Drug Interactions (7.1) and Clinical Pharmacology (12.3)].

3 DOSAGE FORMS AND STRENGTHS

Round tablet contains pioglitazone as follows:

- 15 mg: White to off-white, debossed with "ACTOS" on one side and "15" on the other
- 30 mg: White to off-white, debossed with "ACTOS" on one side and "30" on the other
- 45 mg: White to off-white, debossed with "ACTOS" on one side and "45" on the other

4 CONTRAINDICATIONS

- Initiation in patients with established NYHA Class III or IV heart failure [see Boxed Warning].
- Use in patients with known hypersensitivity to pioglitazone or any other component of ACTOS.

5 WARNINGS AND PRECAUTIONS

5.1 Congestive Heart Failure

ACTOS, like other thiazolidinediones, can cause dose-related fluid retention when used alone or in combination with other antidiabetic medications and is most common when ACTOS is used in combination with insulin. Fluid retention may lead to or exacerbate congestive heart failure. Patients should be observed for signs and symptoms of congestive heart failure. If congestive heart failure develops, it should be managed according to current standards of care and discontinuation or dose reduction of ACTOS must be considered [see Boxed Warning, Contraindications (4), and Adverse Reactions (6.1)].

5.2 Hypoglycemia

Patients receiving ACTOS in combination with insulin or other antidiabetic medications (particularly insulin secretagogues such as sulfonylureas) may be at risk for hypoglycemia. A reduction in the dose of the concomitant antidiabetic medication may be necessary to reduce the risk of hypoglycemia [see Dosage and Administration (2.2)].

5.3 Hepatic Effects

There have been postmarketing reports of fatal and non-fatal hepatic failure in patients taking ACTOS, although the reports contain insufficient information necessary to establish the probable cause. There has been no evidence of drug-induced hepatotoxicity in the ACTOS controlled clinical trial database to date [see Adverse Reactions (6.1)].

Patients with type 2 diabetes may have fatty liver disease or cardiac disease with episodic congestive heart failure, both of which may cause liver test abnormalities, and they may also have other forms of liver disease, many of which can be treated or managed. Therefore, obtaining a liver test panel (serum alanine aminotransferase [ALT], aspartate aminotransferase [AST], alkaline phosphatase, and total bilirubin) and assessing the patient is recommended before initiating ACTOS therapy. In patients with abnormal liver tests, ACTOS should be initiated with caution.

Measure liver tests promptly in patients who report symptoms that may indicate liver injury, including fatigue, anorexia, right upper abdominal discomfort, dark urine or jaundice. In this clinical context, if the patient is found to have abnormal liver tests (ALT greater than 3 times the upper limit of the reference range), ACTOS treatment should be interrupted and investigation done to establish the probable cause. ACTOS should not be restarted in these patients without another explanation for the liver test abnormalities.

Patients who have serum ALT greater than three times the reference range with serum total bilirubin greater than two times the reference range without alternative etiologies are at risk for severe drug-induced liver injury, and should not be restarted on ACTOS. For patients with lesser elevations of serum ALT or bilirubin and with an alternate probable cause, treatment with ACTOS can be used with caution.

5.4 Urinary Bladder Tumors

Tumors were observed in the urinary bladder of male rats in the two-year carcinogenicity study [see Nonclinical Toxicology (13.1)]. In addition, during the three year PROactive clinical trial, 14 patients out of 2605 (0.54%) randomized to ACTOS and 5 out of 2633 (0.19%) randomized to placebo were diagnosed with bladder cancer. After excluding patients in whom exposure to study drug was less than one year at the time of diagnosis of bladder cancer, there were 6 (0.23%) cases on ACTOS and two (0.08%) cases on placebo. After completion of the trial, a large subset of patients was observed for up to 10 additional years, with little additional exposure to ACTOS. During the 13 years of both PROactive and observational follow-up, the occurrence of bladder cancer did not differ between patients randomized to ACTOS or placebo (HR =1.00; [95% CI: 0.59−1.72]).

Findings regarding the risk of bladder cancer in patients exposed to ACTOS vary among observational studies; some did not find an increased risk of bladder cancer associated with ACTOS, while others did.

A large prospective10-year observational cohort study conducted in the United States found no statistically significant increase in the risk of bladder cancer in diabetic patients ever exposed to ACTOS, compared to those never exposed to ACTOS (HR =1.06 [95% CI 0.89−1.26]).

A retrospective cohort study conducted with data from the United Kingdom found a statistically significant association between ever exposure to ACTOS and bladder cancer (HR: 1.63; [95% CI: 1.22−2.19]).

Associations between cumulative dose or cumulative duration of exposure to ACTOS and bladder cancer were not detected in some studies including the 10-year observational study in the U.S., but were in others. Inconsistent findings and limitations inherent in these and other studies preclude conclusive interpretations of the observational data.

ACTOS may be associated with an increase in the risk of urinary bladder tumors. There are insufficient data to determine whether pioglitazone is a tumor promoter for urinary bladder tumors.

Consequently, ACTOS should not be used in patients with active bladder cancer and the benefits of glycemic control versus unknown risks for cancer recurrence with ACTOS should be considered in patients with a prior history of bladder cancer.

5.5 Edema

In controlled clinical trials, edema was reported more frequently in patients treated with ACTOS than in placebo-treated patients and is dose-related [see Adverse Reactions (6.1)]. In postmarketing experience, reports of new onset or worsening edema have been received.

ACTOS should be used with caution in patients with edema. Because thiazolidinediones, including ACTOS, can cause fluid retention, which can exacerbate or lead to congestive heart failure, ACTOS should be used with caution in patients at risk for congestive heart failure. Patients treated with ACTOS should be monitored for signs and symptoms of congestive heart failure [see Boxed Warning, Warnings and Precautions (5.1) and Patient Counseling Information (17)].

5.6 Fractures

In PROactive (the Prospective Pioglitazone Clinical Trial in Macrovascular Events), 5238 patients with type 2 diabetes and a history of macrovascular disease were randomized to ACTOS (N=2605), force-titrated up to 45 mg daily or placebo (N=2633) in addition to standard of care. During a mean follow-up of 34.5 months, the incidence of bone fracture in females was 5.1% (44/870) for ACTOS versus 2.5% (23/905) for placebo. This difference was noted after the first year of treatment and persisted during the course of the study. The majority of fractures observed in female patients were nonvertebral fractures including lower limb and distal upper limb. No increase in the incidence of fracture was observed in men treated with ACTOS (1.7%) versus placebo (2.1%). The risk of fracture should be considered in the care of patients, especially female patients, treated with ACTOS and attention should be given to assessing and maintaining bone health according to current standards of care.

5.7 Macular Edema

Macular edema has been reported in postmarketing experience in diabetic patients who were taking ACTOS or another thiazolidinedione. Some patients presented with blurred vision or decreased visual acuity, but others were diagnosed on routine ophthalmologic examination.

Most patients had peripheral edema at the time macular edema was diagnosed. Some patients had improvement in their macular edema after discontinuation of the thiazolidinedione.

Patients with diabetes should have regular eye exams by an ophthalmologist according to current standards of care. Patients with diabetes who report any visual symptoms should be promptly referred to an ophthalmologist, regardless of the patient's underlying medications or other physical findings [see Adverse Reactions (6.1)].

5.8 Macrovascular Outcomes

There have been no clinical studies establishing conclusive evidence of macrovascular risk reduction with ACTOS.

6 ADVERSE REACTIONS

The following serious adverse reactions are discussed elsewhere in the labeling:

- Congestive heart failure [see Boxed Warning and Warnings and Precautions (5.1)]
- Edema [see Warnings and Precautions (5.5)]
- Fractures [see Warnings and Precautions (5.6)]

6.1 Clinical Trials Experience

Because clinical trials are conducted under widely varying conditions, adverse reaction rates observed in the clinical trials of a drug cannot be directly compared to rates in the clinical trials of another drug and may not reflect the rates observed in practice.

Over 8500 patients with type 2 diabetes have been treated with ACTOS in randomized, double-blind, controlled clinical trials, including 2605 patients with type 2 diabetes and macrovascular disease treated with ACTOS in the PROactive clinical trial. In these trials, over 6000 patients have been treated with ACTOS for six months or longer, over 4500 patients have been treated with ACTOS for one year or longer, and over 3000 patients have been treated with ACTOS for at least two years.

In six pooled 16- to 26-week placebo-controlled monotherapy and 16- to 24-week add-on combination therapy trials, the incidence of withdrawals due to adverse events was 4.5% for patients treated with ACTOS and 5.8% for comparator-treated patients. The most common adverse events leading to withdrawal were related to inadequate glycemic control, although the incidence of these events was lower (1.5%) with ACTOS than with placebo (3.0%).

In the PROactive trial, the incidence of withdrawals due to adverse events was 9.0% for patients treated with ACTOS and 7.7% for placebo-treated patients. Congestive heart failure was the most common serious adverse event leading to withdrawal occurring in 1.3% of patients treated with ACTOS and 0.6% of patients treated with placebo.

Common Adverse Events: 16- to 26-Week Monotherapy Trials

A summary of the incidence and type of common adverse events reported in three pooled 16- to 26-week placebo-controlled monotherapy trials of ACTOS is provided in Table 1. Terms that are reported represent those that occurred at an incidence of >5% and more commonly in patients treated with ACTOS than in patients who received placebo. None of these adverse events were related to ACTOS dose.

Table 1. Three Pooled 16- to 26-Week Placebo-Controlled Clinical Trials of ACTOS Monotherapy: Adverse Events Reported at an Incidence >5% and More Commonly in Patients Treated with ACTOS than in Patients Treated with Placebo
% of Patients
 | Placebo N=259 | ACTOS N=606
Upper Respiratory Tract Infection | 8.5 | 13.2
Headache | 6.9 | 9.1
Sinusitis | 4.6 | 6.3
Myalgia | 2.7 | 5.4
Pharyngitis | 0.8 | 5.1

Common Adverse Events: 16- to 24-Week Add-on Combination Therapy Trials

A summary of the overall incidence and types of common adverse events reported in trials of ACTOS add-on to sulfonylurea is provided in Table 2. Terms that are reported represent those that occurred at an incidence of >5% and more commonly with the highest tested dose of ACTOS.

Table 2. 16- to 24-Week Clinical Trials of ACTOS Add-on to Sulfonylurea
 | 16-Week Placebo-Controlled Trial Adverse Events Reported in >5% of Patients and More Commonly in Patients Treated with ACTOS 30 mg + Sulfonylurea than in Patients Treated with Placebo + Sulfonylurea
 | % of Patients
 | Placebo + Sulfonylurea N=187 | ACTOS 15 mg + Sulfonylurea N=184 | ACTOS 30 mg + Sulfonylurea N=189
Edema | 2.1 | 1.6 | 12.7
Headache | 3.7 | 4.3 | 5.3
Flatulence | 0.5 | 2.7 | 6.3
Weight Increased | 0 | 2.7 | 5.3
 | 24-Week Non-Controlled Double-Blind Trial Adverse Events Reported in >5% of Patients and More Commonly in Patients Treated with ACTOS 45 mg + Sulfonylurea than in Patients Treated with ACTOS 30 mg + Sulfonylurea
 | % of Patients
 | ACTOS 30 mg + Sulfonylurea N=351 |  | ACTOS 45 mg + Sulfonylurea N=351
Hypoglycemia | 13.4 |  | 15.7
Edema | 10.5 |  | 23.1
Upper Respiratory Tract Infection | 12.3 |  | 14.8
Weight Increased | 9.1 |  | 13.4
Urinary Tract Infection | 5.7 |  | 6.8
Note: The preferred terms of edema peripheral, generalized edema, pitting edema and fluid retention were combined to form the aggregate term of "edema."

A summary of the overall incidence and types of common adverse events reported in trials of ACTOS add-on to metformin is provided in Table 3. Terms that are reported represent those that occurred at an incidence of >5% and more commonly with the highest tested dose of ACTOS.

Table 3. 16- to 24-Week Clinical Trials of ACTOS Add-on to Metformin
 | 16-Week Placebo-Controlled Trial Adverse Events Reported in >5% of Patients and More Commonly in Patients Treated with ACTOS + Metformin than in Patients Treated with Placebo + Metformin
 | % of Patients
 | Placebo + Metformin N=160 | ACTOS 30 mg + Metformin N=168
Edema | 2.5 | 6.0
Headache | 1.9 | 6.0
 | 24-Week Non-Controlled Double-Blind Trial; Adverse Events Reported in >5% of Patients and More Commonly in Patients Treated with ACTOS 45 mg + Metformin than in Patients Treated with ACTOS 30 mg + Metformin
 | % of Patients
 | ACTOS 30 mg + Metformin N=411 | ACTOS 45 mg + Metformin N=416
Upper Respiratory Tract Infection | 12.4 | 13.5
Edema | 5.8 | 13.9
Headache | 5.4 | 5.8
Weight Increased | 2.9 | 6.7
Note: The preferred terms of edema peripheral, generalized edema, pitting edema and fluid retention were combined to form the aggregate term of "edema."

Table 4 summarizes the incidence and types of common adverse events reported in trials of ACTOS add-on to insulin. Terms that are reported represent those that occurred at an incidence of >5% and more commonly with the highest tested dose of ACTOS.

Table 4. 16- to 24-Week Clinical Trials of ACTOS Add-on to Insulin
 | 16-Week Placebo-Controlled Trial Adverse Events Reported in >5% of Patients and More Commonly in Patients Treated with ACTOS 30 mg + Insulin than in Patients Treated with Placebo + Insulin
 | % of Patients
 | Placebo + Insulin N=187 | ACTOS 15 mg + Insulin N=191 | ACTOS 30 mg + Insulin N=188
Hypoglycemia | 4.8 | 7.9 | 15.4
Edema | 7.0 | 12.6 | 17.6
Upper Respiratory Tract Infection | 9.6 | 8.4 | 14.9
Headache | 3.2 | 3.1 | 6.9
Weight Increased | 0.5 | 5.2 | 6.4
Back Pain | 4.3 | 2.1 | 5.3
Dizziness | 3.7 | 2.6 | 5.3
Flatulence | 1.6 | 3.7 | 5.3
 | 24-Week Non-Controlled Double-Blind Trial Adverse Events Reported in >5% of Patients and More Commonly in Patients Treated with ACTOS 45 mg + Insulin than in Patients Treated with ACTOS 30 mg + Insulin
 | % of Patients
 | ACTOS 30 mg + Insulin N=345 |  | ACTOS 45 mg + Insulin N=345
Hypoglycemia | 43.5 |  | 47.8
Edema | 22.0 |  | 26.1
Weight Increased | 7.2 |  | 13.9
Urinary Tract Infection | 4.9 |  | 8.7
Diarrhea | 5.5 |  | 5.8
Back Pain | 3.8 |  | 6.4
Blood Creatine Phosphokinase Increased | 4.6 |  | 5.5
Sinusitis | 4.6 |  | 5.5
Hypertension | 4.1 |  | 5.5
Note: The preferred terms of edema peripheral, generalized edema, pitting edema and fluid retention were combined to form the aggregate term of "edema."

A summary of the overall incidence and types of common adverse events reported in the PROactive trial is provided in Table 5. Terms that are reported represent those that occurred at an incidence of >5% and more commonly in patients treated with ACTOS than in patients who received placebo.

Table 5. PROactive Trial: Incidence and Types of Adverse Events Reported in >5% of Patients Treated with ACTOS and More Commonly than Placebo
 | % of Patients
 | Placebo N=2633 | ACTOS N=2605
Hypoglycemia | 18.8 | 27.3
Edema | 15.3 | 26.7
Cardiac Failure | 6.1 | 8.1
Pain in Extremity | 5.7 | 6.4
Back Pain | 5.1 | 5.5
Chest Pain | 5.0 | 5.1
Mean duration of patient follow-up was 34.5 months.

Congestive Heart Failure

A summary of the incidence of adverse events related to congestive heart failure is provided in Table 6 for the 16- to 24-week add-on to sulfonylurea trials, for the 16- to 24-week add-on to insulin trials, and for the 16- to 24-week add-on to metformin trials. None of the events were fatal.

Table 6. Treatment-Emergent Adverse Events of Congestive Heart Failure (CHF)
Patients Treated with ACTOS or Placebo Added on to a Sulfonylurea
 | Number (%) of Patients
 | Placebo-Controlled Trial (16 weeks) |  |  | Non-Controlled; Double-Blind Trial (24 weeks)
 | Placebo + Sulfonylurea N=187 | ACTOS 15 mg + Sulfonylurea N=184 | ACTOS 30 mg + Sulfonylurea N=189 | ACTOS 30 mg + Sulfonylurea N=351 | ACTOS 45 mg + Sulfonylurea N=351
At least one congestive heart failure event | 2 (1.1%) | 0 | 0 | 1 (0.3%) | 6 (1.7%)
Hospitalized | 2 (1.1%) | 0 | 0 | 0 | 2 (0.6%)
Patients Treated with ACTOS or Placebo Added on to Insulin
 | Number (%) of Patients
 | Placebo-Controlled Trial (16 weeks) |  |  | Non-Controlled Double-Blind Trial (24 weeks)
 | Placebo + Insulin N=187 | ACTOS 15 mg + Insulin N=191 | ACTOS 30 mg + Insulin N=188 | ACTOS 30 mg + Insulin N=345 | ACTOS 45 mg + Insulin N=345
At least one congestive heart failure event | 0 | 2 (1.0%) | 2 (1.1%) | 3 (0.9%) | 5 (1.4%)
Hospitalized | 0 | 2 (1.0%) | 1 (0.5%) | 1 (0.3%) | 3 (0.9%)
Patients Treated with ACTOS or Placebo Added on to Metformin
 | Number (%) of Patients
 | Placebo-Controlled Trial (16 weeks) |  |  | Non-Controlled Double-Blind Trial (24 weeks)
 | Placebo + Metformin N=160 |  | ACTOS 30 mg + Metformin N=168 | ACTOS 30 mg + Metformin N=411 | ACTOS 45 mg + Metformin N=416
At least one congestive heart failure event | 0 |  | 1 (0.6%) | 0 | 1 (0.2%)
Hospitalized | 0 |  | 1 (0.6%) | 0 | 1 (0.2%)

Patients with type 2 diabetes and NYHA class II or early class III congestive heart failure were randomized to receive 24 weeks of double-blind treatment with either ACTOS at daily doses of 30 mg to 45 mg (n=262) or glyburide at daily doses of 10 mg to 15 mg (n=256). A summary of the incidence of adverse events related to congestive heart failure reported in this study is provided in Table 7.

Table 7. Treatment-Emergent Adverse Events of Congestive Heart Failure (CHF) in Patients with NYHA Class II or III Congestive Heart Failure Treated with ACTOS or Glyburide
 | Number (%) of Subjects
 | ACTOS N=262 | Glyburide N=256
Death due to cardiovascular causes (adjudicated) | 5 (1.9%) | 6 (2.3%)
Overnight hospitalization for worsening CHF (adjudicated) | 26 (9.9%) | 12 (4.7%)
Emergency room visit for CHF (adjudicated) | 4 (1.5%) | 3 (1.2%)
Patients experiencing CHF progression during study | 35 (13.4%) | 21 (8.2%)

Congestive heart failure events leading to hospitalization that occurred during the PROactive trial are summarized in Table 8.

Table 8. Treatment-Emergent Adverse Events of Congestive Heart Failure (CHF) in PROactive Trial
 | Number (%) of Patients
 | Placebo N=2633 | ACTOS N=2605
At least one hospitalized congestive heart failure event | 108 (4.1%) | 149 (5.7%)
Fatal | 22 (0.8%) | 25 (1.0%)
Hospitalized, nonfatal | 86 (3.3%) | 124 (4.7%)

Cardiovascular Safety

In the PROactive trial, 5238 patients with type 2 diabetes and a history of macrovascular disease were randomized to ACTOS (N=2605), force-titrated up to 45 mg daily or placebo (N=2633) in addition to standard of care. Almost all patients (95%) were receiving cardiovascular medications (beta blockers, ACE inhibitors, angiotensin II receptor blockers, calcium channel blockers, nitrates, diuretics, aspirin, statins and fibrates). At baseline, patients had a mean age of 62 years, mean duration of diabetes of 9.5 years, and mean HbA1c of 8.1%. Mean duration of follow-up was 34.5 months.

The primary objective of this trial was to examine the effect of ACTOS on mortality and macrovascular morbidity in patients with type 2 diabetes mellitus who were at high risk for macrovascular events. The primary efficacy variable was the time to the first occurrence of any event in a cardiovascular composite endpoint that included all-cause mortality, nonfatal myocardial infarction (MI) including silent MI, stroke, acute coronary syndrome, cardiac intervention including coronary artery bypass grafting or percutaneous intervention, major leg amputation above the ankle, and bypass surgery or revascularization in the leg. A total of 514 (19.7%) patients treated with ACTOS and 572 (21.7%) placebo-treated patients experienced at least one event from the primary composite endpoint (hazard ratio 0.90; 95% Confidence Interval: 0.80, 1.02; p=0.10).

Although there was no statistically significant difference between ACTOS and placebo for the three-year incidence of a first event within this composite, there was no increase in mortality or in total macrovascular events with ACTOS. The number of first occurrences and total individual events contributing to the primary composite endpoint is shown in Table 9.

Table 9. PROactive: Number of First and Total Events for Each Component within the Cardiovascular Composite Endpoint
Cardiovascular Events | Placebo N=2633 |  | ACTOS N=2605
Cardiovascular Events | First Events n (%) | Total events n | First Events n (%) | Total events n
Any event | 572 (21.7) | 900 | 514 (19.7) | 803
All-cause mortality | 122 (4.6) | 186 | 110 (4.2) | 177
Nonfatal myocardial infarction (MI) | 118 (4.5) | 157 | 105 (4.0) | 131
Stroke | 96 (3.6) | 119 | 76 (2.9) | 92
Acute coronary syndrome | 63 (2.4) | 78 | 42 (1.6) | 65
Cardiac intervention (CABG/PCI) | 101 (3.8) | 240 | 101 (3.9) | 195
Major leg amputation | 15 (0.6) | 28 | 9 (0.3) | 28
Leg revascularization | 57 (2.2) | 92 | 71 (2.7) | 115
CABG = coronary artery bypass grafting; PCI = percutaneous intervention

Weight Gain

Dose-related weight gain occurs when ACTOS is used alone or in combination with other antidiabetic medications. The mechanism of weight gain is unclear but probably involves a combination of fluid retention and fat accumulation.

Tables 10 and 11 summarize the changes in body weight with ACTOS and placebo in the 16- to 26-week randomized, double-blind monotherapy and 16- to 24-week combination add-on therapy trials and in the PROactive trial.

Table 10. Weight Changes (kg) from Baseline During Randomized, Double-Blind Clinical Trials
 |  | Control Group (Placebo) | ACTOS 15 mg | ACTOS 30 mg | ACTOS 45 mg
 |  | Median (25th/75th percentile) | Median (25th/75th percentile) | Median (25th/75th percentile) | Median (25th/75th percentile)
Monotherapy (16 to 26 weeks) |  | -1.4 (-2.7/0.0) N=256 | 0.9 (-0.5/3.4) N=79 | 1.0 (-0.9/3.4) N=188 | 2.6 (0.2/5.4) N=79
Combination Therapy (16 to 24 weeks) | Sulfonylurea | -0.5 (-1.8/0.7) N=187 | 2.0 (0.2/3.2) N=183 | 3.1 (1.1/5.4) N=528 | 4.1 (1.8/7.3) N=333
Combination Therapy (16 to 24 weeks) | Metformin | -1.4 (-3.2/0.3) N=160 | N/A | 0.9 (-1.3/3.2) N=567 | 1.8 (-0.9/5.0) N=407
Combination Therapy (16 to 24 weeks) | Insulin | 0.2 (-1.4/1.4) N=182 | 2.3 (0.5/4.3) N=190 | 3.3 (0.9/6.3) N=522 | 4.1 (1.4/6.8) N=338

Table 11. Median Change in Body Weight in Patients Treated with ACTOS Versus Patients Treated with Placebo During the Double-Blind Treatment Period in the PROactive Trial
 | Placebo | ACTOS
 | Median; (25th/75th; percentile) | Median; (25th/75th; percentile)
Change from baseline to final visit (kg) | -0.5 (-3.3, 2.0); N=2581 | +3.6 (0.0, 7.5); N=2560
Note: Median exposure for both ACTOS and Placebo was 2.7 years.

Edema

Edema induced from taking ACTOS is reversible when ACTOS is discontinued. The edema usually does not require hospitalization unless there is coexisting congestive heart failure. A summary of the frequency and types of edema adverse events occurring in clinical investigations of ACTOS is provided in Table 12.

Table 12. Adverse Events of Edema in Patients Treated with ACTOS
 |  | Number (%) of Patients
 |  | Placebo | ACTOS 15 mg | ACTOS 30 mg | ACTOS 45 mg
Monotherapy (16 to 26 weeks) |  | 3 (1.2%) N=259 | 2 (2.5%) N= 81 | 13 (4.7%) N= 275 | 11 (6.5%) N=169
Combined Therapy (16 to 24 weeks) | Sulfonylurea | 4 (2.1%) N=187 | 3 (1.6%) N=184 | 61 (11.3%) N=540 | 81 (23.1%) N=351
Combined Therapy (16 to 24 weeks) | Metformin | 4 (2.5%) N=160 | N/A | 34 (5.9%) N=579 | 58 (13.9%) N=416
Combined Therapy (16 to 24 weeks) | Insulin | 13 (7.0%) N=187 | 24 (12.6%) N=191 | 109 (20.5%) N=533 | 90 (26.1%) N=345
Note: The preferred terms of edema peripheral, generalized edema, pitting edema and fluid retention were combined to form the aggregate term of "edema."

Table 13. Adverse Events of Edema in Patients in the PROactive Trial
Number (%) of Patients
Placebo N=2633 | ACTOS N=2605
419 (15.9%) | 712 (27.3%)
Note: The preferred terms of edema peripheral, generalized edema, pitting edema and fluid retention were combined to form the aggregate term of "edema."

Hepatic Effects

There has been no evidence of induced hepatotoxicity with ACTOS in the ACTOS controlled clinical trial database to date. One randomized, double-blind 3-year trial comparing ACTOS to glyburide as add-on to metformin and insulin therapy was specifically designed to evaluate the incidence of serum ALT elevation to greater than three times the upper limit of the reference range, measured every eight weeks for the first 48 weeks of the trial then every 12 weeks thereafter. A total of 3/1051 (0.3%) patients treated with ACTOS and 9/1046 (0.9%) patients treated with glyburide developed ALT values greater than three times the upper limit of the reference range. None of the patients treated with ACTOS in the ACTOS controlled clinical trial database to date have had a serum ALT greater than three times the upper limit of the reference range and a corresponding total bilirubin greater than two times the upper limit of the reference range, a combination predictive of the potential for severe drug-induced liver injury.

Hypoglycemia

In the ACTOS clinical trials, adverse events of hypoglycemia were reported based on clinical judgment of the investigators and did not require confirmation with fingerstick glucose testing.

In the 16-week add-on to sulfonylurea trial, the incidence of reported hypoglycemia was 3.7% with ACTOS 30 mg and 0.5% with placebo. In the 16-week add-on to insulin trial, the incidence of reported hypoglycemia was 7.9% with ACTOS 15 mg, 15.4% with ACTOS 30 mg, and 4.8% with placebo.

The incidence of reported hypoglycemia was higher with ACTOS 45 mg compared to ACTOS 30 mg in both the 24-week add-on to sulfonylurea trial (15.7% vs. 13.4%) and in the 24-week add-on to insulin trial (47.8% vs. 43.5%).

Three patients in these four trials were hospitalized due to hypoglycemia. All three patients were receiving ACTOS 30 mg (0.9%) in the 24-week add-on to insulin trial. An additional 14 patients reported severe hypoglycemia (defined as causing considerable interference with patient's usual activities) that did not require hospitalization. These patients were receiving ACTOS 45 mg in combination with sulfonylurea (n=2) or ACTOS 30 mg or 45 mg in combination with insulin (n=12).

Urinary Bladder Tumors

Tumors were observed in the urinary bladder of male rats in the two-year carcinogenicity study [see Nonclinical Toxicology (13.1)]. During the three year PROactive clinical trial, 14 patients out of 2605 (0.54%) randomized to ACTOS and 5 out of 2633 (0.19%) randomized to placebo were diagnosed with bladder cancer. After excluding patients in whom exposure to study drug was less than one year at the time of diagnosis of bladder cancer, there were 6 (0.23%) cases on ACTOS and two (0.08%) cases on placebo. After completion of the trial, a large subset of patients was observed for up to 10 additional years, with little additional exposure to ACTOS. During the 13 years of both PROactive and observational follow-up, the occurrence of bladder cancer did not differ between patients randomized to ACTOS or placebo (HR =1.00; 95% CI: 0.59-1.72) [see Warnings and Precautions (5.4)].

Laboratory Abnormalities

Hematologic Effects

ACTOS may cause decreases in hemoglobin and hematocrit. In placebo-controlled monotherapy trials, mean hemoglobin values declined by 2% to 4% in patients treated with ACTOS compared with a mean change in hemoglobin of -1% to +1% in placebo-treated patients. These changes primarily occurred within the first 4 to 12 weeks of therapy and remained relatively constant thereafter. These changes may be related to increased plasma volume associated with ACTOS therapy and are not likely to be associated with any clinically significant hematologic effects.

Creatine Phosphokinase

During protocol-specified measurement of serum creatine phosphokinase (CPK) in ACTOS clinical trials, an isolated elevation in CPK to greater than 10 times the upper limit of the reference range was noted in nine (0.2%) patients treated with ACTOS (values of 2150 to 11400 IU/L) and in no comparator-treated patients. Six of these nine patients continued to receive ACTOS, two patients were noted to have the CPK elevation on the last day of dosing and one patient discontinued ACTOS due to the elevation. These elevations resolved without any apparent clinical sequelae. The relationship of these events to ACTOS therapy is unknown.

6.2 Postmarketing Experience

The following adverse reactions have been identified during post-approval use of ACTOS. Because these reactions are reported voluntarily from a population of uncertain size, it is generally not possible to reliably estimate their frequency or establish a causal relationship to drug exposure.

- New onset or worsening diabetic macular edema with decreased visual acuity [see Warnings and Precautions (5.7)].
- Fatal and nonfatal hepatic failure [see Warnings and Precautions (5.3)].

Postmarketing reports of congestive heart failure have been reported in patients treated with ACTOS, both with and without previously known heart disease and both with and without concomitant insulin administration.

In postmarketing experience, there have been reports of unusually rapid increases in weight and increases in excess of that generally observed in clinical trials. Patients who experience such increases should be assessed for fluid accumulation and volume-related events such as excessive edema and congestive heart failure [see Boxed Warning and Warnings and Precautions (5.1)].

7 DRUG INTERACTIONS

7.1 Strong CYP2C8 Inhibitors

An inhibitor of CYP2C8 (e.g., gemfibrozil) significantly increases the exposure (area under the serum concentration-time curve or AUC) and half-life (t1/2) of pioglitazone. Therefore, the maximum recommended dose of ACTOS is 15 mg daily if used in combination with gemfibrozil or other strong CYP2C8 inhibitors [see Dosage and Administration (2.3) and Clinical Pharmacology (12.3)].

7.2 CYP2C8 Inducers

An inducer of CYP2C8 (e.g., rifampin) may significantly decrease the exposure (AUC) of pioglitazone. Therefore, if an inducer of CYP2C8 is started or stopped during treatment with ACTOS, changes in diabetes treatment may be needed based on clinical response without exceeding the maximum recommended daily dose of 45 mg for ACTOS [see Clinical Pharmacology (12.3)].

7.3 Topiramate

A decrease in the exposure of pioglitazone and its active metabolites were noted with concomitant administration of pioglitazone and topiramate [see Clinical Pharmacology (12.3)]. The clinical relevance of this decrease is unknown; however, when ACTOS and topiramate are used concomitantly, monitor patients for adequate glycemic control.

8 USE IN SPECIFIC POPULATIONS

8.1 Pregnancy

Risk Summary

Limited data with ACTOS in pregnant women are not sufficient to determine a drug-associated risk for major birth defects or miscarriage. There are risks to the mother and fetus associated with poorly controlled diabetes in pregnancy [see Clinical Considerations].

In animal reproduction studies, no adverse developmental effects were observed when pioglitazone was administered to pregnant rats and rabbits during organogenesis at exposures up to 5- and 35-times the 45 mg clinical dose, respectively, based on body surface area [see Data].

The estimated background risk of major birth defects is 6-10% in women with pre-gestational diabetes with a HbA1c >7 and has been reported to be as high as 20-25% in women with a HbA1c >10. The estimated background risk of miscarriage for the indicated population is unknown. In the U.S. general population, the estimated background risk of major birth defects and miscarriage in clinically recognized pregnancies is 2-4% and 15-20%, respectively.

Clinical Considerations

Disease-associated maternal and/or embryo/fetal risk

Poorly controlled diabetes in pregnancy increases the maternal risk for diabetic ketoacidosis, pre-eclampsia, spontaneous abortions, preterm delivery, still birth and delivery complications. Poorly controlled diabetes increases the fetal risk for major birth defects, still birth, and macrosomia related morbidity.

Data

Animal Data

Pioglitazone administered to pregnant rats during organogenesis did not cause adverse developmental effects at a dose of 20 mg/kg (~5-times the 45 mg clinical dose), but delayed parturition and reduced embryofetal viability at 40 and 80 mg/kg, or ≥9-times the 45 mg clinical dose, by body surface area. In pregnant rabbits administered pioglitazone during organogenesis, no adverse developmental effects were observed at 80 mg/kg (~35-times the 45 mg clinical dose), but reduced embryofetal viability at 160 mg/kg, or ~69-times the 45 mg clinical dose, by body surface area. When pregnant rats received pioglitazone during late gestation and lactation, delayed postnatal development, attributed to decreased body weight, occurred in offspring at maternal doses of 10 mg/kg and above or ≥2 times the 45 mg clinical dose, by body surface area.

8.2 Lactation

Risk Summary

There is no information regarding the presence of pioglitazone in human milk, the effects on the breastfed infant, or the effects on milk production. Pioglitazone is present in rat milk; however due to species-specific differences in lactation physiology, animal data may not reliably predict drug levels in human milk. The developmental and health benefits of breastfeeding should be considered along with the mother's clinical need for ACTOS and any potential adverse effects on the breastfed infant from ACTOS or from the underlying maternal condition.

8.3 Females and Males of Reproductive Potential

Discuss the potential for unintended pregnancy with premenopausal women as therapy with ACTOS, like other thiazolidinediones, may result in ovulation in some anovulatory women.

8.4 Pediatric Use

Safety and effectiveness of ACTOS in pediatric patients have not been established.

ACTOS is not recommended for use in pediatric patients based on adverse effects observed in adults, including fluid retention and congestive heart failure, fractures, and urinary bladder tumors [see Warnings and Precautions (5.1, 5.4, 5.5, and 5.6)].

8.5 Geriatric Use

A total of 92 patients (15.2%) treated with ACTOS in the three pooled 16- to 26-week double-blind, placebo-controlled, monotherapy trials were ≥65 years old and two patients (0.3%) were ≥75 years old. In the two pooled 16- to 24-week add-on to sulfonylurea trials, 201 patients (18.7%) treated with ACTOS were ≥65 years old and 19 (1.8%) were ≥75 years old. In the two pooled 16- to 24-week add-on to metformin trials, 155 patients (15.5%) treated with ACTOS were ≥65 years old and 19 (1.9%) were ≥75 years old. In the two pooled 16- to 24-week add-on to insulin trials, 272 patients (25.4%) treated with ACTOS were ≥65 years old and 22 (2.1%) were ≥75 years old.

In PROactive, 1068 patients (41.0%) treated with ACTOS were ≥65 years old and 42 (1.6%) were ≥75 years old.

In pharmacokinetic studies with pioglitazone, no significant differences were observed in pharmacokinetic parameters between elderly and younger patients [see Clinical Pharmacology (12.3)].

Although clinical experiences have not identified differences in effectiveness and safety between the elderly (≥65 years) and younger patients, these conclusions are limited by small sample sizes for patients ≥75 years old.

10 OVERDOSAGE

During controlled clinical trials, one case of overdose with ACTOS was reported. A male patient took 120 mg per day for four days, then 180 mg per day for seven days. The patient denied any clinical symptoms during this period.

In the event of overdosage, appropriate supportive treatment should be initiated according to the patient's clinical signs and symptoms.

11 DESCRIPTION

ACTOS tablets are a thiazolidinedione and an agonist for peroxisome proliferator-activated receptor (PPAR) gamma that contains an oral antidiabetic medication: pioglitazone.

Pioglitazone [(±)-5-[[4-[2-(5-ethyl-2-pyridinyl) ethoxy] phenyl] methyl]-2,4-] thiazolidinedione monohydrochloride contains one asymmetric carbon, and the compound is synthesized and used as the racemic mixture. The two enantiomers of pioglitazone interconvert in vivo. No differences were found in the pharmacologic activity between the two enantiomers. The structural formula is as shown:

Pioglitazone hydrochloride is an odorless white crystalline powder that has a molecular formula of C19H20N2O3S•HCl and a molecular weight of 392.90 daltons. It is soluble in N,N-dimethylformamide, slightly soluble in anhydrous ethanol, very slightly soluble in acetone and acetonitrile, practically insoluble in water, and insoluble in ether.

ACTOS is available as a tablet for oral administration containing 15 mg, 30 mg, or 45 mg of pioglitazone (as the base) formulated with the following excipients: lactose monohydrate NF, hydroxypropylcellulose NF, carboxymethylcellulose calcium NF, and magnesium stearate NF.

12 CLINICAL PHARMACOLOGY

12.1 Mechanism of Action

ACTOS is a thiazolidinedione that depends on the presence of insulin for its mechanism of action. ACTOS decreases insulin resistance in the periphery and in the liver resulting in increased insulin-dependent glucose disposal and decreased hepatic glucose output. Pioglitazone is not an insulin secretagogue. Pioglitazone is an agonist for peroxisome proliferator-activated receptor-gamma (PPARγ). PPAR receptors are found in tissues important for insulin action such as adipose tissue, skeletal muscle, and liver. Activation of PPARγ nuclear receptors modulates the transcription of a number of insulin responsive genes involved in the control of glucose and lipid metabolism.

In animal models of diabetes, pioglitazone reduces the hyperglycemia, hyperinsulinemia, and hypertriglyceridemia characteristic of insulin-resistant states such as type 2 diabetes. The metabolic changes produced by pioglitazone result in increased responsiveness of insulin-dependent tissues and are observed in numerous animal models of insulin resistance.

Because pioglitazone enhances the effects of circulating insulin (by decreasing insulin resistance), it does not lower blood glucose in animal models that lack endogenous insulin.

12.2 Pharmacodynamics

Clinical studies demonstrate that ACTOS improves insulin sensitivity in insulin-resistant patients. ACTOS enhances cellular responsiveness to insulin, increases insulin-dependent glucose disposal and improves hepatic sensitivity to insulin. In patients with type 2 diabetes, the decreased insulin resistance produced by ACTOS results in lower plasma glucose concentrations, lower plasma insulin concentrations, and lower HbA1c values. In controlled clinical trials, ACTOS had an additive effect on glycemic control when used in combination with a sulfonylurea, metformin, or insulin [see Clinical Studies (14.2)].

Patients with lipid abnormalities were included in clinical trials with ACTOS. Overall, patients treated with ACTOS had mean decreases in serum triglycerides, mean increases in HDL cholesterol, and no consistent mean changes in LDL and total cholesterol. There is no conclusive evidence of macrovascular benefit with ACTOS [see Warnings and Precautions (5.8) and Adverse Reactions (6.1)].

In a 26-week, placebo-controlled, dose-ranging monotherapy study, mean serum triglycerides decreased in the 15 mg, 30 mg, and 45 mg ACTOS dose groups compared to a mean increase in the placebo group. Mean HDL cholesterol increased to a greater extent in patients treated with ACTOS than in the placebo-treated patients. There were no consistent differences for LDL and total cholesterol in patients treated with ACTOS compared to placebo (see Table 14).

Table 14. Lipids in a 26-Week Placebo-Controlled Monotherapy Dose-Ranging Study
 | Placebo | ACTOS 15 mg Once Daily | ACTOS 30 mg Once Daily | ACTOS 45 mg Once Daily
Triglycerides (mg/dL) | N=79 | N=79 | N=84 | N=77
Baseline (mean) | 263 | 284 | 261 | 260
Percent change from baseline (adjusted mean [Adjusted for baseline, pooled center, and pooled center by treatment interaction]) | 4.8% | -9.0% [p<0.05 versus placebo] | -9.6% | -9.3%
HDL Cholesterol (mg/dL) | N=79 | N=79 | N=83 | N=77
Baseline (mean) | 42 | 40 | 41 | 41
Percent change from baseline (adjusted mean) | 8.1% | 14.1% | 12.2% | 19.1%
LDL Cholesterol (mg/dL) | N=65 | N=63 | N=74 | N=62
Baseline (mean) | 139 | 132 | 136 | 127
Percent change from baseline (adjusted mean) | 4.8% | 7.2% | 5.2% | 6.0%
Total Cholesterol (mg/dL) | N=79 | N=79 | N=84 | N=77
Baseline (mean) | 225 | 220 | 223 | 214
Percent change from baseline (adjusted mean) | 4.4% | 4.6% | 3.3% | 6.4%

In the two other monotherapy studies (16 weeks and 24 weeks) and in combination therapy studies with sulfonylurea (16 weeks and 24 weeks), metformin (16 weeks and 24 weeks) or insulin (16 weeks and 24 weeks), the results were generally consistent with the data above.

12.3 Pharmacokinetics

Following once-daily administration of ACTOS, steady-state serum concentrations of both pioglitazone and its major active metabolites, M-III (keto derivative of pioglitazone) and M-IV (hydroxyl derivative of pioglitazone), are achieved within seven days. At steady-state, M-III and M-IV reach serum concentrations equal to or greater than that of pioglitazone. At steady-state, in both healthy volunteers and patients with type 2 diabetes, pioglitazone comprises approximately 30% to 50% of the peak total pioglitazone serum concentrations (pioglitazone plus active metabolites) and 20% to 25% of the total AUC.

Cmax, AUC, and trough serum concentrations (Cmin) for pioglitazone and M-III and M-IV, increased proportionally with administered doses of 15 mg and 30 mg per day.

Absorption

Following oral administration of pioglitazone, Tmax of pioglitazone was within two hours. Food delays the Tmax to three to four hours but does not alter the extent of absorption (AUC).

Distribution

The mean apparent volume of distribution (Vd/F) of pioglitazone following single-dose administration is 0.63 ± 0.41 (mean ± SD) L/kg of body weight. Pioglitazone is extensively protein bound (>99%) in human serum, principally to serum albumin. Pioglitazone also binds to other serum proteins, but with lower affinity. M-III and M-IV are also extensively bound (>98%) to serum albumin.

Metabolism

Pioglitazone is extensively metabolized by hydroxylation and oxidation; the metabolites also partly convert to glucuronide or sulfate conjugates. Metabolites M-III and M-IV are the major circulating active metabolites in humans.

In vitro data demonstrate that multiple CYP isoforms are involved in the metabolism of pioglitazone, which include CYP2C8 and, to a lesser degree, CYP3A4 with additional contributions from a variety of other isoforms including the mainly extrahepatic CYP1A1. In vivo study of pioglitazone in combination with gemfibrozil, a strong CYP2C8 inhibitor, showed that pioglitazone is a CYP2C8 substrate [see Dosage and Administration (2.3) and Drug Interactions (7)]. Urinary 6ß-hydroxycortisol/cortisol ratios measured in patients treated with ACTOS showed that pioglitazone is not a strong CYP3A4 enzyme inducer.

Excretion and Elimination

Following oral administration, approximately 15% to 30% of the pioglitazone dose is recovered in the urine. Renal elimination of pioglitazone is negligible, and the drug is excreted primarily as metabolites and their conjugates. It is presumed that most of the oral dose is excreted into the bile either unchanged or as metabolites and eliminated in the feces.

The mean serum half-life (t1/2) of pioglitazone and its metabolites (M-III and M-IV) range from three to seven hours and 16 to 24 hours, respectively. Pioglitazone has an apparent clearance, CL/F, calculated to be five to seven L/hr.

Renal Impairment

The serum elimination half-life of pioglitazone, M-III, and M-IV remains unchanged in patients with moderate (creatinine clearance [CLcr] 30 to 50 mL/min) and severe (CLcr <30 mL/min) renal impairment when compared to subjects with normal renal function. Therefore, no dose adjustment in patients with renal impairment is required.

Hepatic Impairment

Compared with healthy controls, subjects with impaired hepatic function (Child-Turcotte-Pugh Grade B/C) have an approximate 45% reduction in pioglitazone and total pioglitazone (pioglitazone, M-III, and M-IV) mean Cmax but no change in the mean AUC values. Therefore, no dose adjustment in patients with hepatic impairment is required.

There are postmarketing reports of liver failure with ACTOS and clinical trials have generally excluded patients with serum ALT >2.5 times the upper limit of the reference range. Use caution in patients with liver disease [see Warnings and Precautions (5.3)].

Geriatric Patients

In healthy elderly subjects, Cmax of pioglitazone was not significantly different, but AUC values were approximately 21% higher than those achieved in younger subjects. The mean t1/2 of pioglitazone was also prolonged in elderly subjects (about ten hours) as compared to younger subjects (about seven hours). These changes were not of a magnitude that would be considered clinically relevant.

Pediatric Patients

Safety and efficacy of pioglitazone in pediatric patients have not been established. ACTOS is not recommended for use in pediatric patients [see Use in Specific Populations (8.4)].

Gender

The mean Cmax and AUC values of pioglitazone were increased 20% to 60% in women compared to men. In controlled clinical trials, HbA1c decreases from baseline were generally greater for females than for males (average mean difference in HbA1c 0.5%). Because therapy should be individualized for each patient to achieve glycemic control, no dose adjustment is recommended based on gender alone.

Ethnicity

Pharmacokinetic data among various ethnic groups are not available.

Drug-Drug Interactions

Table 15. Effect of Pioglitazone Coadministration on Systemic Exposure of Other Drugs
 | Coadministered Drug
Pioglitazone Dosage Regimen (mg) [Daily for 7 days unless otherwise noted] | Name and Dose Regimens | Change in AUC [% change (with/without coadministered drug and no change = 0%); symbols of ↑ and ↓ indicate the exposure increase and decrease, respectively] |  | Change in Cmax
45 mg (N = 12) | Warfarin [Pioglitazone had no clinically significant effect on prothrombin time]
45 mg (N = 12) | Daily loading then maintenance doses based PT and INR values Quick's Value = 35 ± 5% | R-Warfarin | ↓3% | R-Warfarin | ↓2%
45 mg (N = 12) | Daily loading then maintenance doses based PT and INR values Quick's Value = 35 ± 5% | S-Warfarin | ↓1% | S-Warfarin | ↑1%
45 mg (N = 12) | Digoxin
45 mg (N = 12) | 0.200 mg twice daily (loading dose) then 0.250 mg daily (maintenance dose, 7 days) | ↑15% |  | ↑17%
45 mg daily for 21 days (N = 35) | Oral Contraceptive
45 mg daily for 21 days (N = 35) | [Ethinyl Estradiol (EE) 0.035 mg plus Norethindrone (NE) 1 mg] for 21 days | EE | ↓11% | EE | ↓13%
45 mg daily for 21 days (N = 35) | [Ethinyl Estradiol (EE) 0.035 mg plus Norethindrone (NE) 1 mg] for 21 days | NE | ↑3% | NE | ↓7%
45 mg (N = 23) | Fexofenadine
45 mg (N = 23) | 60 mg twice daily for 7 days | ↑30% |  | ↑37%
45 mg (N = 14) | Glipizide
45 mg (N = 14) | 5 mg daily for 7 days | ↓3% |  | ↓8%
45 mg daily for 8 days (N = 16) | Metformin
45 mg daily for 8 days (N = 16) | 1000 mg single dose on Day 8 | ↓3% |  | ↓5%
45 mg (N = 21) | Midazolam
45 mg (N = 21) | 7.5 mg single dose on Day 15 | ↓26% |  | ↓26%
45 mg (N = 24) | Ranitidine
45 mg (N = 24) | 150 mg twice daily for 7 days | ↑1% |  | ↓1%
45 mg daily for 4 days (N = 24) | Nifedipine ER
45 mg daily for 4 days (N = 24) | 30 mg daily for 4 days | ↓13% |  | ↓17%
45 mg (N = 25) | Atorvastatin Ca
45 mg (N = 25) | 80 mg daily for 7 days | ↓14% |  | ↓23%
45 mg (N = 22) | Theophylline
45 mg (N = 22) | 400 mg twice daily for 7 days | ↑2% |  | ↑5%

Table 16. Effect of Coadministered Drugs on Pioglitazone Systemic Exposure
Coadministered Drug and Dosage Regimen | Pioglitazone
Coadministered Drug and Dosage Regimen | Dose Regimen (mg) [Daily for 7 days unless otherwise noted] | Change in AUC [Mean ratio (with/without coadministered drug and no change = 1-fold) % change (with/without coadministered drug and no change = 0%); symbols of ↑ and ↓ indicate the exposure increase and decrease, respectively] | Change in Cmax
Gemfibrozil 600 mg twice daily for 2 days (N = 12) | 15 mg single dose | ↑3.2-fold [The half-life of pioglitazone increased from 8.3 hours to 22.7 hours in the presence of gemfibrozil [see Dosage and Administration (2.3) and Drug Interactions (7.1)]] | ↑6%
Ketoconazole 200 mg twice daily for 7 days (N = 28) | 45 mg | ↑34% | ↑14%
Rifampin 600 mg daily for 5 days (N = 10) | 30 mg single dose | ↓54% | ↓5%
Fexofenadine 60 mg twice daily for 7 days (N = 23) | 45 mg | ↑1% | 0%
Ranitidine 150 mg twice daily for 4 days (N = 23) | 45 mg | ↓13% | ↓16%
Nifedipine ER 30 mg daily for 7 days (N = 23) | 45 mg | ↑5% | ↑4%
Atorvastatin Ca 80 mg daily for 7 days (N = 24) | 45 mg | ↓24% | ↓31%
Theophylline 400 mg twice daily for 7 days (N = 22) | 45 mg | ↓4% | ↓2%
Topiramate 96 mg twice daily for 7 days [Indicates duration of concomitant administration with highest twice-daily dose of topiramate from Day 14 onwards over the 22 days of study] (N = 26) | 30 mg | ↓15% [Additional decrease in active metabolites; 60% for M-III and 16% for M-IV] | 0%

13 NONCLINICAL TOXICOLOGY

13.1 Carcinogenesis, Mutagenesis, Impairment of Fertility

A two-year carcinogenicity study was conducted in male and female rats at oral doses up to 63 mg/kg (approximately 14 times the maximum recommended human oral dose of 45 mg based on mg/m^2). Drug-induced tumors were not observed in any organ except for the urinary bladder of male rats. Benign and/or malignant transitional cell neoplasms were observed in male rats at 4 mg/kg/day and above (approximately equal to the maximum recommended human oral dose based on mg/m^2). Urinary calculi with subsequent irritation and hyperplasia were postulated as the mechanism for bladder tumors observed in male rats. A two-year mechanistic study in male rats utilizing dietary acidification to reduce calculi formation was completed in 2009. Dietary acidification decreased but did not abolish the hyperplastic changes in the bladder. The presence of calculi exacerbated the hyperplastic response to pioglitazone but was not considered the primary cause of the hyperplastic changes.

The relevance to humans of the bladder findings in the male rat cannot be excluded.

A two-year carcinogenicity study was also conducted in male and female mice at oral doses up to 100 mg/kg/day (approximately 11 times the maximum recommended human oral dose based on mg/m^2). No drug-induced tumors were observed in any organ.

Pioglitazone hydrochloride was not mutagenic in a battery of genetic toxicology studies, including the Ames bacterial assay, a mammalian cell forward gene mutation assay (CHO/HPRT and AS52/XPRT), an in vitro cytogenetics assay using CHL cells, an unscheduled DNA synthesis assay, and an in vivo micronucleus assay.

No adverse effects upon fertility were observed in male and female rats at oral doses up to 40 mg/kg pioglitazone hydrochloride daily prior to and throughout mating and gestation (approximately nine times the maximum recommended human oral dose based on mg/m^2).

13.2 Animal Toxicology and/or Pharmacology

Heart enlargement has been observed in mice (100 mg/kg), rats (4 mg/kg and above) and dogs (3 mg/kg) treated orally with pioglitazone hydrochloride (approximately 11, 1, and 2 times the maximum recommended human oral dose for mice, rats, and dogs, respectively, based on mg/m^2). In a one-year rat study, drug-related early death due to apparent heart dysfunction occurred at an oral dose of 160 mg/kg/day (approximately 35 times the maximum recommended human oral dose based on mg/m^2). Heart enlargement was seen in a 13-week study in monkeys at oral doses of 8.9 mg/kg and above (approximately four times the maximum recommended human oral dose based on mg/m^2), but not in a 52-week study at oral doses up to 32 mg/kg (approximately 13 times the maximum recommended human oral dose based on mg/m^2).

14 CLINICAL STUDIES

14.1 Monotherapy

Three randomized, double-blind, placebo-controlled trials with durations from 16 to 26 weeks were conducted to evaluate the use of ACTOS as monotherapy in patients with type 2 diabetes. These trials examined ACTOS at doses up to 45 mg or placebo once daily in a total of 865 patients.

In a 26-week dose-ranging monotherapy trial, 408 patients with type 2 diabetes were randomized to receive 7.5 mg, 15 mg, 30 mg, or 45 mg of ACTOS, or placebo once daily. Therapy with any previous antidiabetic agent was discontinued eight weeks prior to the double-blind period. Treatment with 15 mg, 30 mg, and 45 mg of ACTOS produced statistically significant improvements in HbA1c and fasting plasma glucose (FPG) at endpoint compared to placebo (see Figure 1, Table 17).

Figure 1 shows the time course for changes in HbA1c in this 26-week study.

Figure 1. Mean Change from Baseline for HbA1c in a 26-Week Placebo-Controlled Dose-Ranging Study (Observed Values)

Table 17. Glycemic Parameters in a 26-Week Placebo-Controlled Dose-Ranging Monotherapy Trial
 | Placebo | ACTOS 15 mg Once Daily | ACTOS 30 mg Once Daily | ACTOS 45 mg Once Daily
Total Population
HbA1c (%) | N=79 | N=79 | N=85 | N=76
Baseline (mean) | 10.4 | 10.2 | 10.2 | 10.3
Change from baseline (adjusted mean [Adjusted for baseline, pooled center, and pooled center by treatment interaction]) | 0.7 | -0.3 | -0.3 | -0.9
Difference from placebo (adjusted mean) 95% Confidence Interval |  | -1.0 [p ≤0.05 vs. placebo] (-1.6, -0.4) | -1.0 (-1.6, -0.4) | -1.6 (-2.2, -1.0)
Fasting Plasma Glucose (mg/dL) | N=79 | N=79 | N=84 | N=77
Baseline (mean) | 268 | 267 | 269 | 276
Change from baseline (adjusted mean) | 9 | -30 | -32 | -56
Difference from placebo (adjusted mean) 95% Confidence Interval |  | -39 (-63, -16) | -41 (-64, -18) | -65 (-89, -42)

In a 24-week placebo-controlled monotherapy trial, 260 patients with type 2 diabetes were randomized to one of two forced-titration ACTOS treatment groups or a mock-titration placebo group. Therapy with any previous antidiabetic agent was discontinued six weeks prior to the double-blind period. In one ACTOS treatment group, patients received an initial dose of 7.5 mg once daily. After four weeks, the dose was increased to 15 mg once daily and after another four weeks, the dose was increased to 30 mg once daily for the remainder of the trial (16 weeks). In the second ACTOS treatment group, patients received an initial dose of 15 mg once daily and were titrated to 30 mg once daily and 45 mg once daily in a similar manner. Treatment with ACTOS, as described, produced statistically significant improvements in HbA1c and FPG at endpoint compared to placebo (see Table 18).

Table 18. Glycemic Parameters in a 24-Week Placebo-Controlled Forced-Titration Monotherapy Trial
 | Placebo | ACTOS 30 mg [Final dose in forced titration] Once Daily | ACTOS 45 mg Once Daily
Total Population
HbA1c (%) | N=83 | N=85 | N=85
Baseline (mean) | 10.8 | 10.3 | 10.8
Change from baseline (adjusted mean [Adjusted for baseline, pooled center, and pooled center by treatment interaction]) | 0.9 | -0.6 | -0.6
Difference from placebo (adjusted mean) 95% Confidence Interval |  | -1.5 [p ≤0.05 vs. placebo] (-2.0, -1.0) | -1.5 (-2.0, -1.0)
Fasting Plasma Glucose (mg/dL) | N=78 | N=82 | N=85
Baseline (mean) | 279 | 268 | 281
Change from baseline (adjusted mean) | 18 | -44 | -50
Difference from placebo (adjusted mean) 95% Confidence Interval |  | -62 (-82, -0.41) | -68 (-88, -0.48)

In a 16-week monotherapy trial, 197 patients with type 2 diabetes were randomized to treatment with 30 mg of ACTOS or placebo once daily. Therapy with any previous antidiabetic agent was discontinued six weeks prior to the double-blind period. Treatment with 30 mg of ACTOS produced statistically significant improvements in HbA1c and FPG at endpoint compared to placebo (see Table 19).

Table 19. Glycemic Parameters in a 16-Week Placebo-Controlled Monotherapy Trial
 | Placebo | ACTOS 30 mg Once Daily
Total Population
HbA1c (%) | N=93 | N=100
Baseline (mean) | 10.3 | 10.5
Change from baseline (adjusted mean [Adjusted for baseline, pooled center, and pooled center by treatment interaction]) | 0.8 | -0.6
Difference from placebo (adjusted mean) 95% Confidence Interval |  | -1.4 [p ≤0.050 vs. placebo] (-1.8, -0.9)
Fasting Plasma Glucose (mg/dL) | N=91 | N=99
Baseline (mean) | 270 | 273
Change from baseline (adjusted mean) | 8 | -50
Difference from placebo (adjusted mean) 95% Confidence Interval |  | -58 (-77, -38)

14.2 Combination Therapy

Three 16-week, randomized, double-blind, placebo-controlled clinical trials were conducted to evaluate the effects of ACTOS (15 mg and/or 30 mg) on glycemic control in patients with type 2 diabetes who were inadequately controlled (HbA1c ≥8%) despite current therapy with a sulfonylurea, metformin, or insulin. In addition, three 24-week randomized, double-blind clinical trials were conducted to evaluate the effects of ACTOS 30 mg vs. ACTOS 45 mg on glycemic control in patients with type 2 diabetes who were inadequately controlled (HbA1c ≥8%) despite current therapy with a sulfonylurea, metformin, or insulin. Previous diabetes treatment may have been monotherapy or combination therapy.

Add-on to Sulfonylurea Trials

Two clinical trials were conducted with ACTOS in combination with a sulfonylurea. Both studies included patients with type 2 diabetes on any dose of a sulfonylurea, either alone or in combination with another antidiabetic agent. All other antidiabetic agents were withdrawn at least three weeks prior to starting study treatment.

In the first study, 560 patients were randomized to receive 15 mg or 30 mg of ACTOS or placebo once daily for 16 weeks in addition to their current sulfonylurea regimen. Treatment with ACTOS as add-on to sulfonylurea produced statistically significant improvements in HbA1c and FPG at endpoint compared to placebo add-on to sulfonylurea (see Table 20).

Table 20. Glycemic Parameters in a 16-Week Placebo-Controlled, Add-on to Sulfonylurea Trial
 | Placebo + Sulfonylurea | ACTOS 15 mg + Sulfonylurea | ACTOS 30 mg + Sulfonylurea
Total Population
HbA1c (%) | N=181 | N=176 | N=182
Baseline (mean) | 9.9 | 10.0 | 9.9
Change from baseline (adjusted mean [Adjusted for baseline, pooled center, and pooled center by treatment interaction]) | 0.1 | -0.8 | -1.2
Difference from placebo +sulfonylurea (adjusted mean) 95% Confidence Interval |  | -0.9 [p≤0.05 vs. placebo + sulfonylurea] (-1.2, -0.6) | -1.3 (-1.6, -1.0)
Fasting Plasma Glucose (mg/dL) | N=182 | N=179 | N=186
Baseline (mean) | 236 | 247 | 239
Change from baseline (adjusted mean) | 6 | -34 | -52
Difference from placebo + sulfonylurea (adjusted mean) 95% Confidence Interval |  | -39 (-52, -27) | -58 (-70, -46)

In the second trial, 702 patients were randomized to receive 30 mg or 45 mg of ACTOS once daily for 24 weeks in addition to their current sulfonylurea regimen. The mean reduction from baseline at Week 24 in HbA1c was 1.6% for the 30 mg dose and 1.7% for the 45 mg dose (see Table 21). The mean reduction from baseline at Week 24 in FPG was 52 mg/dL for the 30 mg dose and 56 mg/dL for the 45 mg dose.

The therapeutic effect of ACTOS in combination with sulfonylurea was observed in patients regardless of the sulfonylurea dose.

Table 21. Glycemic Parameters in a 24-Week Add-on to Sulfonylurea Trial
 | ACTOS 30 mg + Sulfonylurea | ACTOS 45 mg + Sulfonylurea
Total Population
HbA1c (%) | N=340 | N=332
Baseline (mean) | 9.8 | 9.9
Change from baseline (adjusted mean [Adjusted for baseline, pooled center, and pooled center by treatment interaction]) | -1.6 | -1.7
Difference from 30 mg daily ACTOS + sulfonylurea (adjusted mean) (95% CI) |  | -0.1 (-0.4, 0.1)
Fasting Plasma Glucose (mg/dL) | N=338 | N=329
Baseline (mean) | 214 | 217
Change from baseline (adjusted mean) | -52 | -56
Difference from 30 mg daily ACTOS + sulfonylurea (adjusted mean) (95% CI) |  | -5 (-12, 3)
95% CI = 95% confidence interval

Add-on to Metformin Trials

Two clinical trials were conducted with ACTOS in combination with metformin. Both trials included patients with type 2 diabetes on any dose of metformin, either alone or in combination with another antidiabetic agent. All other antidiabetic agents were withdrawn at least three weeks prior to starting study treatment.

In the first trial, 328 patients were randomized to receive either 30 mg of ACTOS or placebo once daily for 16 weeks in addition to their current metformin regimen. Treatment with ACTOS as add-on to metformin produced statistically significant improvements in HbA1c and FPG at endpoint compared to placebo add-on to metformin (see Table 22).

Table 22. Glycemic Parameters in a 16-Week Placebo-Controlled, Add-on to Metformin Trial
 | Placebo + Metformin | ACTOS 30 mg + Metformin
Total Population
HbA1c (%) | N=153 | N=161
Baseline (mean) | 9.8 | 9.9
Change from baseline (adjusted mean [Adjusted for baseline, pooled center, and pooled center by treatment interaction]) | 0.2 | -0.6
Difference from placebo + metformin (adjusted mean) 95% Confidence Interval |  | -0.8 [p≤0.05 vs. placebo + metformin] (-1.2, -0.5)
Fasting Plasma Glucose (mg/dL) | N=157 | N=165
Baseline (mean) | 260 | 254
Change from baseline (adjusted mean) | -5 | -43
Difference from placebo + metformin (adjusted mean) 95% Confidence Interval |  | -38 (-49, -26)

In the second trial, 827 patients were randomized to receive either 30 mg or 45 mg of ACTOS once daily for 24 weeks in addition to their current metformin regimen. The mean reduction from baseline at Week 24 in HbA1c was 0.8% for the 30 mg dose and 1.0% for the 45 mg dose (see Table 23). The mean reduction from baseline at Week 24 in FPG was 38 mg/dL for the 30 mg dose and 51 mg/dL for the 45 mg dose.

Table 23. Glycemic Parameters in a 24-Week Add-on to Metformin Study
 | ACTOS 30 mg + Metformin | ACTOS 45 mg + Metformin
Total Population
HbA1c (%) | N=400 | N=398
Baseline (mean) | 9.9 | 9.8
Change from baseline (adjusted mean [Adjusted for baseline, pooled center, and pooled center by treatment interaction]) | -0.8 | -1.0
Difference from 30 mg daily ACTOS + Metformin (adjusted mean) (95% CI) |  | -0.2 (-0.5, 0.1)
Fasting Plasma Glucose (mg/dL) | N=398 | N=399
Baseline (mean) | 233 | 232
Change from baseline (adjusted mean) | -38 | -51
Difference from 30 mg daily ACTOS + Metformin (adjusted mean) (95% CI) |  | -12 [p ≤0.05 vs. 30 mg daily ACTOS + metformin] (-21, -4)
95% CI = 95% confidence interval

The therapeutic effect of ACTOS in combination with metformin was observed in patients regardless of the metformin dose.

Add-on to Insulin Trials

Two clinical trials were conducted with ACTOS in combination with insulin. Both trials included patients with type 2 diabetes on insulin, either alone or in combination with another antidiabetic agent. All other antidiabetic agents were withdrawn prior to starting study treatment. In the first trial, 566 patients were randomized to receive either 15 mg or 30 mg of ACTOS or placebo once daily for 16 weeks in addition to their insulin regimen. Treatment with ACTOS as add-on to insulin produced statistically significant improvements in HbA1c and FPG at endpoint compared to placebo add-on to insulin (see Table 24). The mean daily insulin dose at baseline in each treatment group was approximately 70 units. The majority of patients (75% overall, 86% treated with placebo, 77% treated with ACTOS 15 mg, and 61% treated with ACTOS 30 mg) had no change in their daily insulin dose from baseline to the final study visit. The mean change from baseline in daily dose of insulin (including patients with no insulin dose modifications) was -3 units in the patients treated with ACTOS 15 mg, -8 units in the patients treated with ACTOS 30 mg, and -1 unit in patients treated with placebo.

Table 24. Glycemic Parameters in a 16-Week Placebo-Controlled, Add-on to Insulin Trial
 | Placebo + Insulin | ACTOS 15 mg + Insulin | ACTOS 30 mg + Insulin
Total Population
HbA1c (%) | N=177 | N=177 | N=185
Baseline (mean) | 9.8 | 9.8 | 9.8
Change from baseline (adjusted mean [Adjusted for baseline, pooled center, and pooled center by treatment interaction]) | -0.3 | -1.0 | -1.3
Difference from placebo + Insulin (adjusted mean) 95% Confidence Interval |  | -0.7 [p≤0.05 vs. placebo + insulin] (-1.0, -0.5) | -1.0 (-1.3, -0.7)
Fasting Plasma Glucose (mg/dL) | N=179 | N=183 | N=184
Baseline (mean) | 221 | 222 | 229
Change from baseline (adjusted mean) | 1 | -35 | -48
Difference from placebo + Insulin (adjusted mean) 95% Confidence Interval |  | -35 (-51, -19) | -49 (-65, -33)

In the second trial, 690 patients receiving a median of 60 units per day of insulin were randomized to receive either 30 mg or 45 mg of ACTOS once daily for 24 weeks in addition to their current insulin regimen. The mean reduction from baseline at Week 24 in HbA1c was 1.2% for the 30 mg dose and 1.5% for the 45 mg dose. The mean reduction from baseline at Week 24 in FPG was 32 mg/dL for the 30 mg dose and 46 mg/dL for the 45 mg dose (see Table 25). The mean daily insulin dose at baseline in both treatment groups was approximately 70 units. The majority of patients (55% overall, 58% treated with ACTOS 30 mg, and 52% treated with ACTOS 45 mg) had no change in their daily insulin dose from baseline to the final study visit. The mean change from baseline in daily dose of insulin (including patients with no insulin dose modifications) was -5 units in the patients treated with ACTOS 30 mg and -8 units in the patients treated with ACTOS 45 mg.

The therapeutic effect of ACTOS in combination with insulin was observed in patients regardless of the insulin dose.

Table 25. Glycemic Parameters in a 24-Week Add-on to Insulin Trial
 | ACTOS 30 mg + Insulin | ACTOS 45 mg + Insulin
Total Population
HbA1c (%) | N=328 | N=328
Baseline (mean) | 9.9 | 9.7
Change from baseline (adjusted mean [Adjusted for baseline, pooled center, and pooled center by treatment interaction]) | -1.2 | -1.5
Difference from 30 mg daily ACTOS + Insulin (adjusted mean) (95% CI) |  | -0.3 [p ≤0.05 vs. 30 mg daily ACTOS + insulin] (-0.5, -0.1)
Fasting Plasma Glucose (mg/dL) | N=325 | N=327
Baseline (mean) | 202 | 199
Change from baseline (adjusted mean) | -32 | -46
Difference from 30 mg daily ACTOS + Insulin (adjusted mean) (95% CI) |  | -14 (-25, -3)
95% CI = 95% confidence interval

16 HOW SUPPLIED/STORAGE AND HANDLING

ACTOS is available in 15 mg, 30 mg, and 45 mg tablets as follows:

15 mg tablet: White to off-white, round, convex, nonscored tablet with "ACTOS" on one side, and "15" on the other, available in:

NDC 64764-151-04 Bottles of 30
NDC 64764-151-05 Bottles of 90
NDC 64764-151-06 Bottles of 500

30 mg tablet: White to off-white, round, flat, nonscored tablet with "ACTOS" on one side, and "30" on the other, available in:

NDC 64764-301-14 Bottles of 30
NDC 64764-301-15 Bottles of 90
NDC 64764-301-16 Bottles of 500

45 mg tablet: White to off-white, round, flat, nonscored tablet with "ACTOS" on one side, and "45" on the other, available in:

NDC 64764-451-24 Bottles of 30
NDC 64764-451-25 Bottles of 90
NDC 64764-451-26 Bottles of 500

Storage

Store at 25°C (77°F); excursions permitted to 15-30°C (59-86°F) [see USP Controlled Room Temperature]. Keep container tightly closed, and protect from light, moisture and humidity.

17 PATIENT COUNSELING INFORMATION

See FDA-Approved Patient Labeling (Medication Guide).

- It is important to instruct patients to adhere to dietary instructions and to have blood glucose and glycosylated hemoglobin tested regularly. During periods of stress such as fever, trauma, infection, or surgery, medication requirements may change and patients should be reminded to seek medical advice promptly.
- Patients who experience an unusually rapid increase in weight or edema or who develop shortness of breath or other symptoms of heart failure while on ACTOS should immediately report these symptoms to a physician.
- Tell patients to promptly stop taking ACTOS and seek immediate medical advice if there is unexplained nausea, vomiting, abdominal pain, fatigue, anorexia, or dark urine as these symptoms may be due to hepatotoxicity.
- Tell patients to promptly report any sign of macroscopic hematuria or other symptoms such as dysuria or urinary urgency that develop or increase during treatment as these may be due to bladder cancer.
- Tell patients to take ACTOS once daily. ACTOS can be taken with or without meals. If a dose is missed on one day, the dose should not be doubled the following day.
- When using combination therapy with insulin or other antidiabetic medications, the risks of hypoglycemia, its symptoms and treatment, and conditions that predispose to its development should be explained to patients and their family members.
- Inform female patients that treatment with ACTOS, like other thiazolidinediones, may result in an unintended pregnancy in some premenopausal anovulatory females due to its effect on ovulation [see Use in Specific Populations (8.3)].

Distributed by:
Takeda Pharmaceuticals America, Inc.
Cambridge, MA 02142

ACTOS is a registered trademark of Takeda Pharmaceutical Company Limited.

©2025 Takeda Pharmaceuticals America, Inc. All rights reserved.

ACT003 R24

MEDICATION GUIDE

ACTOS® (ak-TŌS)
(pioglitazone) tablets

Read this Medication Guide carefully before you start taking ACTOS and each time you get a refill. There may be new information. This information does not take the place of talking with your doctor about your medical condition or your treatment. If you have any questions about ACTOS, ask your doctor or pharmacist.

What is the most important information I should know about ACTOS?

ACTOS can cause serious side effects, including new or worse heart failure.

- ACTOS can cause your body to keep extra fluid (fluid retention), which leads to swelling (edema) and weight gain. Extra body fluid can make some heart problems worse or lead to heart failure. Heart failure means your heart does not pump blood well enough
- Do not take ACTOS if you have severe heart failure
- If you have heart failure with symptoms (such as shortness of breath or swelling), even if these symptoms are not severe, ACTOS may not be right for you

Call your doctor right away if you have any of the following:

- swelling or fluid retention, especially in the ankles or legs
- shortness of breath or trouble breathing, especially when you lie down
- an unusually fast increase in weight
- unusual tiredness

ACTOS can have other serious side effects. See "What are the possible side effects of ACTOS?"

What is ACTOS?

ACTOS is a prescription medicine used with diet and exercise to improve blood sugar (glucose) control in adults with type 2 diabetes. ACTOS is a diabetes medicine called pioglitazone that may be taken alone or with other diabetes medicines.

It is not known if ACTOS is safe and effective in children under the age of 18.

ACTOS is not recommended for use in children.

ACTOS is not for people with type 1 diabetes.

ACTOS is not for people with diabetic ketoacidosis (increased ketones in your blood or urine).

Who should not take ACTOS?

See "What is the most important information I should know about ACTOS?"

Do not take ACTOS if you:

- have severe heart failure
- are allergic to any of the ingredients in ACTOS. See the end of this Medication Guide for a complete list of ingredients in ACTOS

Talk to your doctor before taking ACTOS if you have either of these conditions.

What should I tell my doctor before taking ACTOS?

Before you take ACTOS, tell your doctor if you:

- have heart failure
- have type 1 ("juvenile") diabetes or had diabetic ketoacidosis
- have a type of diabetic eye disease that causes swelling in the back of the eye (macular edema)
- have liver problems
- have or have had cancer of the bladder
- are pregnant or plan to become pregnant. It is not known if ACTOS can harm your unborn baby. Talk to your doctor if you are pregnant or plan to become pregnant about the best way to control your blood glucose levels while pregnant
- are a premenopausal woman (before the "change of life") who does not have periods regularly or at all. ACTOS may increase your chance of becoming pregnant. Talk to your doctor about birth control choices while taking ACTOS. Tell your doctor right away if you become pregnant while taking ACTOS
- are breastfeeding or plan to breastfeed. It is not known if ACTOS passes into your milk and if it can harm your baby. Talk to your doctor about the best way to control your blood glucose levels while breastfeeding

Tell your doctor about all the medicines you take including prescription and over the counter medicines, vitamins, and herbal supplements.

ACTOS and some of your other medicines can affect each other. You may need to have your dose of ACTOS or certain other medicines changed.

Know the medicines you take. Keep a list of your medicines and show it to your doctor and pharmacist before you start a new medicine. They will tell you if it is okay to take ACTOS with other medicines.

How should I take ACTOS?

- Take ACTOS exactly as your doctor tells you to take it
- Your doctor may change your dose of ACTOS. Do not change your ACTOS dose unless your doctor tells you to
- ACTOS may be prescribed alone or with other diabetes medicines. This will depend on how well your blood sugar is controlled
- Take ACTOS one time each day, with or without food
- If you miss a dose of ACTOS, take your next dose as prescribed unless your doctor tells you differently. Do not take two doses at one time the next day
- If you take too much ACTOS, call your doctor or go to the nearest hospital emergency room right away
- If your body is under stress such as from a fever, infection, accident, or surgery the dose of your diabetes medicines may need to be changed. Call your doctor right away
- Stay on your diet and exercise programs and test your blood sugar regularly while taking ACTOS
- Your doctor should do certain blood tests before you start and while you take ACTOS
- Your doctor should also do hemoglobin A1C testing to check how well your blood sugar is controlled with ACTOS
- Your doctor should check your eyes regularly while you take ACTOS

What are the possible side effects of ACTOS?

ACTOS may cause serious side effects including:

- See "What is the most important information I should know about ACTOS?"
- low blood sugar (hypoglycemia). This can happen if you skip meals, if you also use another medicine that lowers blood sugar, or if you have certain medical problems. Lightheadedness, dizziness, shakiness, or hunger may happen if your blood sugar is too low. Call your doctor if low blood sugar levels are a problem for you
- liver problems. Call your doctor right away if you have:
  - nausea or vomiting
  - stomach pain
  - unusual or unexplained tiredness
  - loss of appetite
  - dark urine
  - yellowing of your skin or the whites of your eyes
- bladder cancer. There may be an increased chance of having bladder cancer when you take ACTOS. You should not take ACTOS if you are receiving treatment for bladder cancer. Tell your doctor right away if you have any of the following symptoms of bladder cancer:
  - blood or a red color in your urine
  - an increased need to urinate
  - pain while you urinate
- broken bones (fractures). Usually in the hand, upper arm, or foot in women. Talk to your doctor for advice on how to keep your bones healthy.
- diabetic eye disease with swelling in the back of the eye (macular edema). Tell your doctor right away if you have any changes in your vision. Your doctor should check your eyes regularly
- release of an egg from an ovary in a woman (ovulation) leading to pregnancy. Ovulation may happen when premenopausal women who do not have regular monthly periods take ACTOS. This can increase your chance of getting pregnant

The most common side effects of ACTOS include:

    - cold-like symptoms (upper respiratory tract infection)
    - headache
    - sinus infection
    - muscle pain
    - sore throat

Tell your doctor if you have any side effect that bothers you or that does not go away. These are not all the side effects of ACTOS. For more information, ask your doctor or pharmacist.

Call your doctor for medical advice about side effects. You may report side effects to FDA at 1-800-FDA-1088.

How should I store ACTOS?

- Store ACTOS at 68°F to 77°F (20°C to 25°C). Keep ACTOS in the original container and protect from light
- Keep the ACTOS bottle tightly closed and keep tablets dry
- Keep ACTOS and all medicines out of the reach of children

General information about the safe and effective use of ACTOS

Medicines are sometimes prescribed for purposes other than those listed in a Medication Guide. Do not use ACTOS for a condition for which it was not prescribed. Do not give ACTOS to other people, even if they have the same symptoms you have. It may harm them.

This Medication Guide summarizes the most important information about ACTOS. If you would like more information, talk with your doctor. You can ask your doctor or pharmacist for information about ACTOS that is written for healthcare professionals. For more information, go to www.actos.com or call 1-877-825-3327.

What are the ingredients in ACTOS?

Active Ingredient: pioglitazone

Inactive Ingredients: lactose monohydrate, hydroxypropylcellulose, carboxymethylcellulose calcium, and magnesium stearate

This Medication Guide has been approved by the U.S. Food and Drug Administration.

Distributed by:
Takeda Pharmaceuticals America, Inc.
Cambridge, MA 02142

Revised: March 2025

ACTOS is a registered trademark of Takeda Pharmaceutical Company Limited.

©2025 Takeda Pharmaceuticals America, Inc. All rights reserved.

ACT003 R24

PRINCIPAL DISPLAY PANEL - 15 mg Tablet Bottle Label

NDC 64764-151-04
30 Tablets

actos®
(pioglitazone)
Tablets

15 mg

Each tablet contains pioglitazone
hydrochloride equivalent to 15 mg
pioglitazone.

Dispense with Medication Guide
available in package insert or at
www.actos.com

Takeda

Rx Only

PRINCIPAL DISPLAY PANEL - 30 mg Tablet Bottle Label

NDC 64764-301-14
30 Tablets

actos®
(pioglitazone)
Tablets

30 mg

Each tablet contains pioglitazone
hydrochloride equivalent to 30 mg
pioglitazone.

Dispense with Medication Guide
available in package insert or at
www.actos.com

Takeda

Rx Only

PRINCIPAL DISPLAY PANEL - 45 mg Tablet Bottle Label

NDC 64764-451-24
30 Tablets

actos®
(pioglitazone)
Tablets

45 mg

Each tablet contains pioglitazone
hydrochloride equivalent to 45 mg
pioglitazone.

Dispense with Medication Guide
available in package insert or at
www.actos.com

Takeda

Rx Only